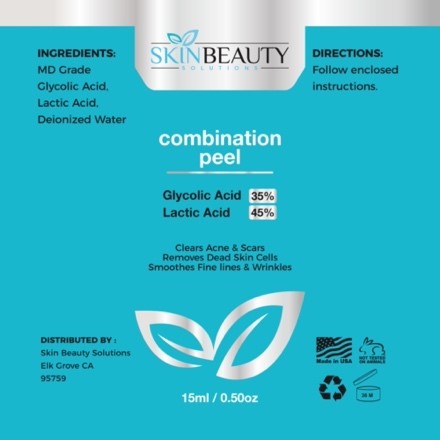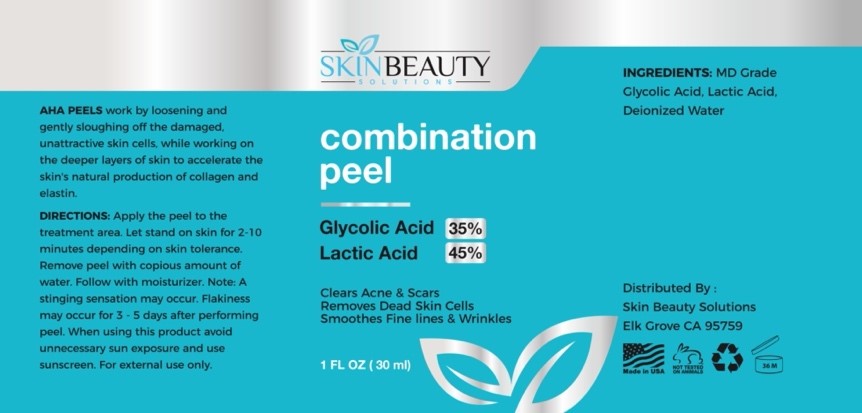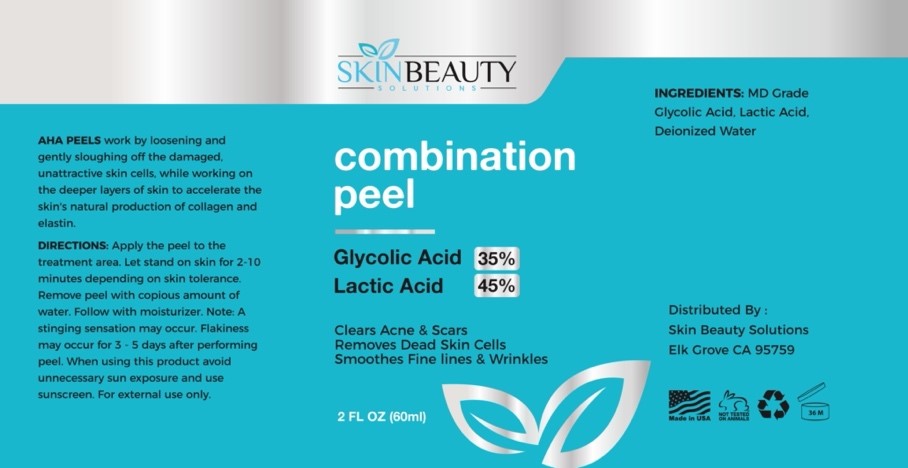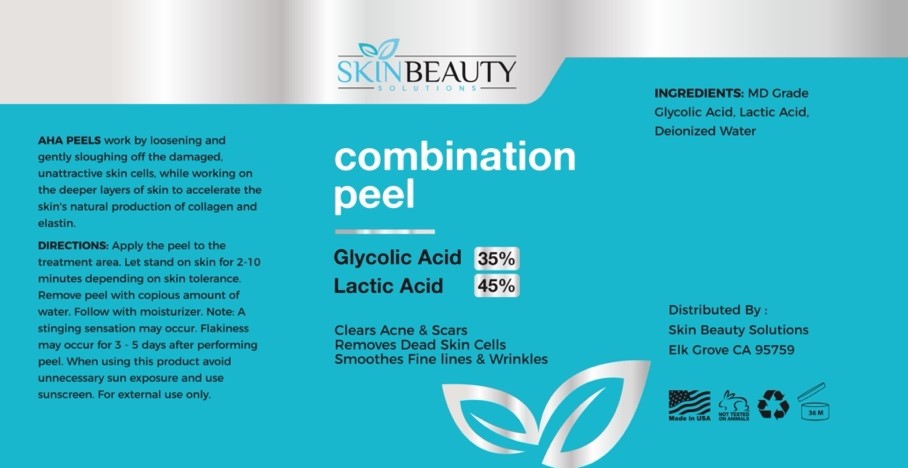 DRUG LABEL: GLYCOLIC 35 / LACTIC 45 Combo Peel
NDC: 84785-0018 | Form: SOLUTION
Manufacturer: Gazebo Wellness SKIN LLC
Category: otc | Type: HUMAN OTC DRUG LABEL
Date: 20241216

ACTIVE INGREDIENTS: LACTIC ACID 0.3 mg/30 mL; GLYCOLIC ACID 0.3 mg/30 mL
INACTIVE INGREDIENTS: WATER

DOSAGE AND ADMINISTRATION

AHA PEELS work by loosening and gently sloughing off the damaged. unattractive skin cells, while working on the deeper layers of skin to accelerate the skin's natural production of collagen and elastin.

WARNINGS

DIRECTIONS: Apply the peel to the treatment area. Let stand on skin for 2-10 minutes depending on skin tolerance. Remove peel with copious amount of water. Follow with moisturizer. Note: A stinging sensation may occur. Flakiness may occur for 3-5 days after performing peel. When using this product avoid unnecessary sun exposure and use sunscreen. For external use only.

Inactive ingredient: Deionized Water.

INDICATIONS AND USAGE

DIRECTIONS: Apply the peel to the treatment area. Let stand on skin for 2-10 minutes depending on skin tolerance. Remove peel with copious amount of water. Follow with moisturizer. Note: A stinging sensation may occur. Flakiness may occur for 3-5 days after performing peel. When using this product avoid unnecessary sun exposure and use sunscreen. For external use only.

keep out of reach of children

PURPOSE

Glycolic Acid 35%
Lactic Acid
45%
Clears Acne & Scars Removes Dead Skin Cells
Smoothes Fine lines & Wrinkles

Distributed By:
Skin Beauty Solutions Elk Grove CA 95759

Active ingredients: MD Grade Glycolic Acid, Lactic Acid.

PACKAGE LABEL

Content of labeling